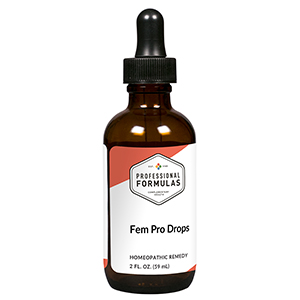 DRUG LABEL: Fem Pro Drops
NDC: 63083-2025 | Form: LIQUID
Manufacturer: Professional Complementary Health Formulas
Category: homeopathic | Type: HUMAN OTC DRUG LABEL
Date: 20190815

ACTIVE INGREDIENTS: CHASTE TREE FRUIT 3 [hp_X]/59 mL; CAULOPHYLLUM THALICTROIDES ROOT 6 [hp_X]/59 mL; BLACK COHOSH 6 [hp_X]/59 mL; RUBUS IDAEUS FRUIT VOLATILE OIL 6 [hp_X]/59 mL; BOS TAURUS PITUITARY GLAND, POSTERIOR 12 [hp_X]/59 mL; BETA-ENDORPHIN HUMAN 30 [hp_X]/59 mL; ESTROGENS, CONJUGATED 30 [hp_X]/59 mL; PROGESTERONE 30 [hp_X]/59 mL
INACTIVE INGREDIENTS: ALCOHOL; WATER

C25

ACTIVE INGREDIENTS

Agnus castus 3X
Caulophyllum thalictroides 6X
Cimicifuga racemosa 6X
Rubus idaeus 6X
Pituitary 12X
Endorphins 30X
Estrogen 30X
Progesterone 30X

QUESTIONS

Professional Formulas

PO Box 2034 Lake Oswego, OR 97035

INDICATIONS

For the temporary relief of painful or heavy menses, abdominal cramping, or backache.*

PURPOSE

*Claims based on traditional homeopathic practice, not accepted medical evidence. Not FDA evaluated.

WARNINGS

In case of overdose, get medical help or contact a poison control center right away.

Keep out of the reach of children.

PREGNANCY OR BREAST FEEDING

If pregnant or breastfeeding, ask a healthcare professional before use.

DIRECTIONS

Place drops under tongue 30 minutes before/after meals. Adults and children 12 years and over: Take 10 drops up to 3 times per day. Consult a physician for use in children under 12 years of age.

OTHER INFORMATION

Tamper resistant. If seal is broken, do not use. After opening, close container tightly and store at room temperature away from heat.

INACTIVE INGREDIENTS

20% ethanol, purified water.

LABEL

Est 1985

Professional Formulas

Complementary Health

Fem Pro Drops

Homeopathic Remedy

2 FL. OZ. (59 mL)